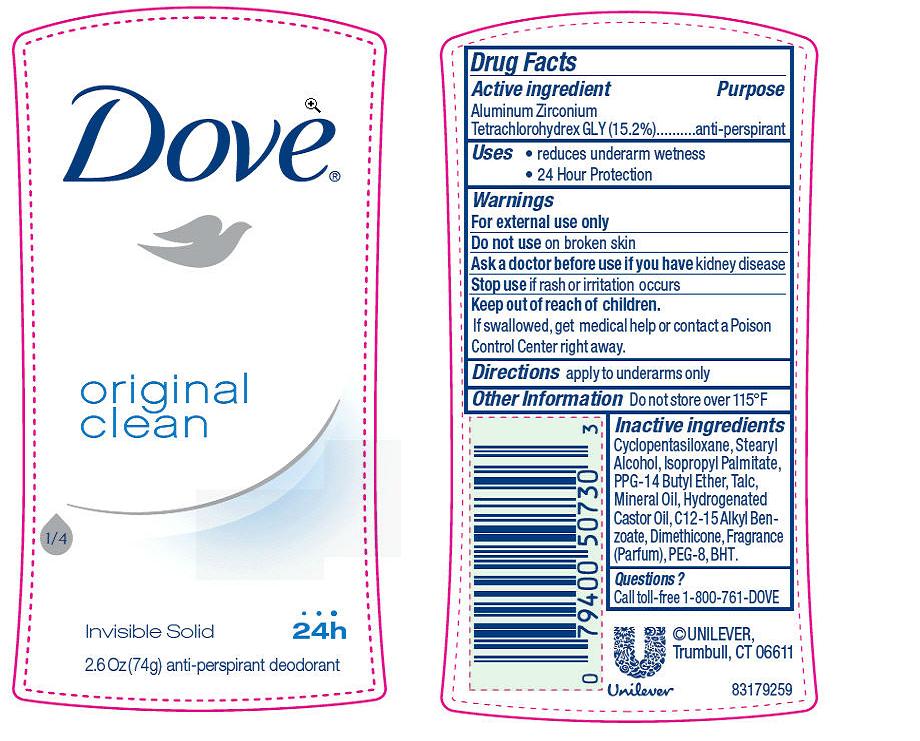 DRUG LABEL: Dove
NDC: 64942-1241 | Form: STICK
Manufacturer: Conopco Inc. d/b/a Unilever
Category: otc | Type: HUMAN OTC DRUG LABEL
Date: 20210813

ACTIVE INGREDIENTS: ALUMINUM ZIRCONIUM TETRACHLOROHYDREX GLY 15.2 g/100 g
INACTIVE INGREDIENTS: CYCLOMETHICONE 5; PPG-14 BUTYL ETHER; STEARYL ALCOHOL; HYDROGENATED CASTOR OIL; DIMETHICONE; BUTYLATED HYDROXYTOLUENE; ISOPROPYL PALMITATE; TALC; ALKYL (C12-15) BENZOATE; MINERAL OIL; POLYETHYLENE GLYCOL 400

Dove Original Clean Antiperspirant deodorant

Active Ingredient

Aluminum Zirconium Tetrachlorohydrex GLY (15.2%)

Purpose

anti-perspirant

Uses

· reduces underarm wetness

· 24 hour protection

Warnings
For External Use Only

Do not use on broken skin

Ask a doctor before use if you have kidney disease

Stop use if rash or irritation occurs

Keep out of reach of children. If swallowed, get medical help or contact a Poison Control Center right away

Directions

· apply to underarms only

Inactive ingredients

Ingredients: Cyclopentasiloxane, Stearyl Alcohol, Isopropyl Palmitate, PPG-14 Butyl Ether, Talc, Mineral Oil, ydrogenated Castor Oil, C12-15 Alkyl Benzoate, Dimethicone, Fragrance (Parfum), PEG-8, BHT.

Questions?

Call toll-free 1-800-761-DOVE

PACKAGE LABEL

2.6 oz PDP